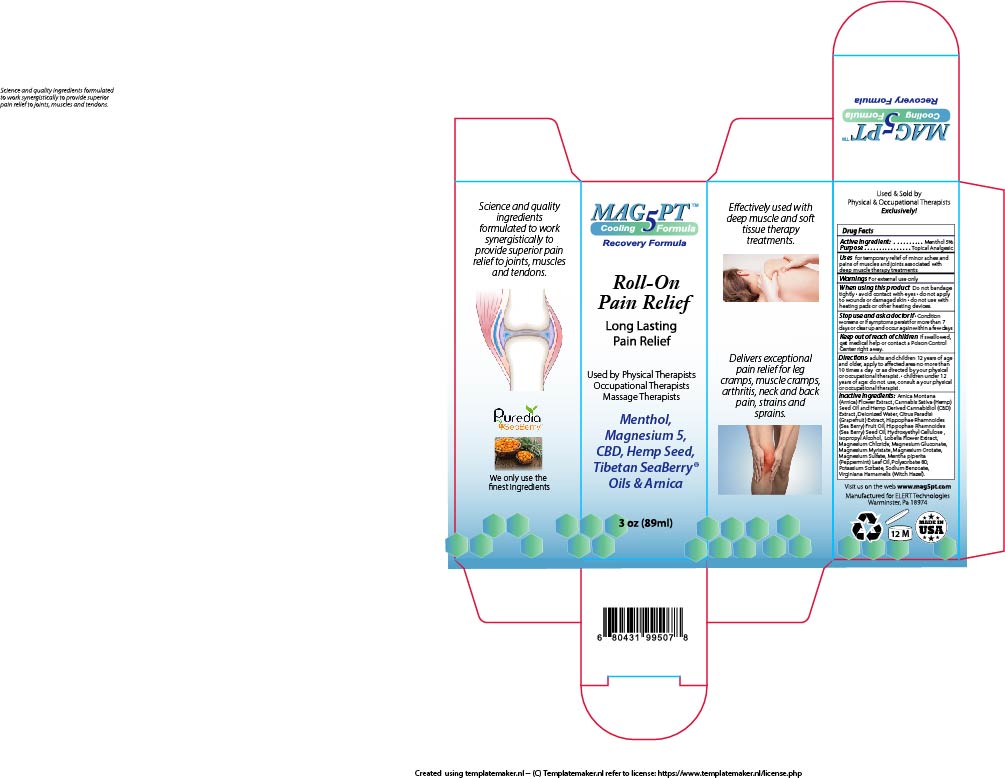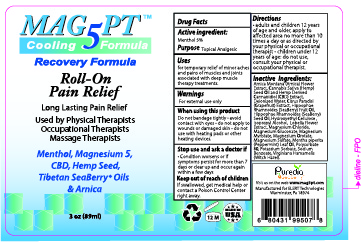 DRUG LABEL: MAG 5 PT ROLL-ON PAIN RELIEF COOLING
NDC: 76348-517 | Form: LIQUID
Manufacturer: RENU LABORATORIES, LLC
Category: otc | Type: HUMAN OTC DRUG LABEL
Date: 20250407

ACTIVE INGREDIENTS: MENTHOL 4.2 g/84 g
INACTIVE INGREDIENTS: MAGNESIUM GLUCONATE ANHYDROUS; MAGNESIUM OROTATE; MAGNESIUM SULFATE; ARNICA MONTANA FLOWER; LOBELIA INFLATA; CANNABIS SATIVA SEED OIL; CANNABIDIOL; MENTHA PIPERITA (PEPPERMINT) OIL; WATER; SODIUM BENZOATE; MAGNESIUM MYRISTATE; POLYSORBATE 80; METHYLCELLULOSE; ISOPROPYL ALCOHOL; HAMAMELIS VIRGINIANA TOP WATER; MAGNESIUM CHLORIDE; POTASSIUM SORBATE

MAG 5 PT ROLL-ON PAIN RELIEF COOLING

Active Ingredient: Menthol 5%

Purpose

Topical analgesic

Uses

For temporary relief of minor aches and pains of muscles and joints associated with deep muscle therapy treatments.

Warnings

For external use only

When using this product

- Do not bandage tightly
- avoid contact with eyes
- do not apply to wounds or damaged skin
- do not use with heating pads or other heating devices

Stop use and ask a doctor if

Condition worsens or if symptoms persist for more than 7 days or clear up and occur again within a few days

Keep out of reach of children

If swallowed, get medical help or contact a Poison Control Center right away.

Directions

Adults and children 12 years of age and older, apply to affected area no more than 10 times a day or as directed by your physical or occupational therapist - children under 12 years of age consult your physical or occupational therapist.

INACTIVE INGREDIENT

Arnica Montana (Arnica) Flower Extract, Butyrospermum Parkii (Shea) Butter, Cannabis Sativa (Hemp) Seed Oil and Hemp Derived Cannabidiol (CBD) Extract, Capsicum Frutescens Fruit Extract, Carthamus Tinctorius (Safflower) Seed Oil, Cetearyl Alcohol, Cetearyl Glucoside, Citrus Paradisi (Grapefruit) Extract, Cocos Nucifera (Coconut) Oil, C13-14 Isoparaffin, Deionized Water, Emulsifying Wax, Hamamelis Virginiana (Witch Hazel), Hippophae Rhamnoides (Sea Berry) Fruit Oil, Hippophae Rhamnoides (Sea Berry) Seed Oil, Laureth-7, Lobelia Flower Extract, Magnesium Chloride, Magnesium Gluconate, Magnesium Myristate, Magnesium Orotate, Magnesium Sulfate, Magifera Indica (Mango) Seed Butter, Mentha piperita (Peppermint) Leaf Oil, Olea Europaea (Olive) Oil, Olus Oil (vegetable), Phenoxyethanol, Polyacrylamide, Xanthan Gum

PACKAGE LABEL

MAG 5 PT COOLING ROLL-ON LABEL AND BOX ART